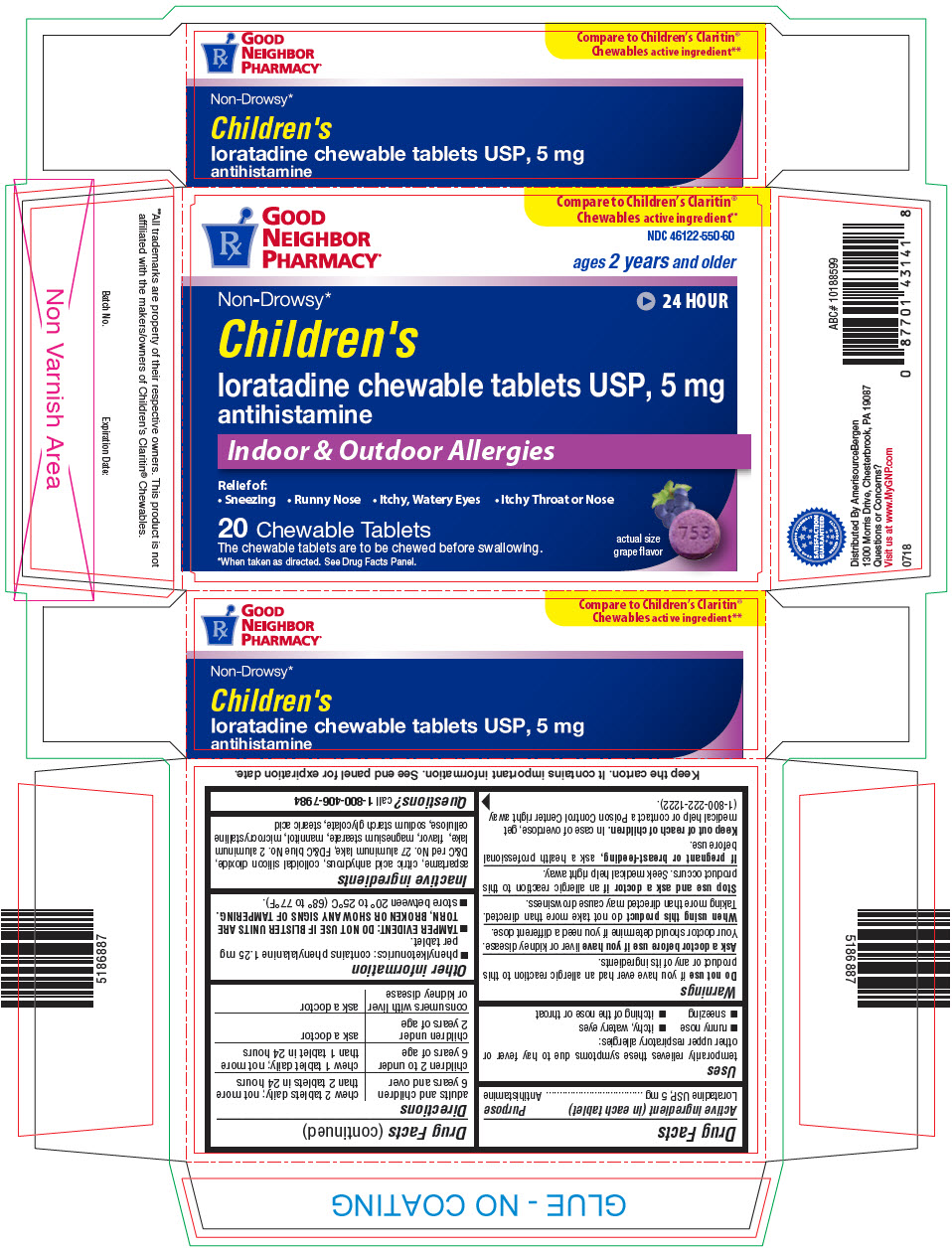 DRUG LABEL: Childrens Loratadine
NDC: 46122-550 | Form: TABLET, CHEWABLE
Manufacturer: Amerisource Bergen
Category: otc | Type: HUMAN OTC DRUG LABEL
Date: 20180807

ACTIVE INGREDIENTS: Loratadine 5 mg/1 1
INACTIVE INGREDIENTS: aspartame; anhydrous citric acid; silicon dioxide; d&c red no. 27; fd&c blue no. 2; magnesium stearate; mannitol; microcrystalline cellulose; stearic acid; sodium starch glycolate type a potato

Children's Loratadine Chewable Tablets USP, 5 mg

Drug Facts

Active ingredient (in each tablet)

Loratadine USP, 5 mg

Purpose

Antihistamine

Uses

temporarily relieves these symptoms due to hay fever or other upper respiratory allergies:

- runny nose
- sneezing
- itchy, watery eyes
- itching of the nose or throat

Warnings

Do not use if you have ever had an allergic reaction to this product or any of its ingredients.

Ask a doctor before use if you have liver or kidney disease. Your doctor should determine if you need a different dose.

When using this product do not take more than directed. Taking more than directed may cause drowsiness.

Stop use and ask a doctor if an allergic reaction to this product occurs. Seek medical help right away.

PREGNANCY OR BREAST FEEDING

If pregnant or breast-feeding, ask a health professional before use.

Keep out of reach of children. In case of overdose, get medical help or contact a Poison Control Center right away (1-800-222-1222).

Directions

adults and children 6 years and over | chew 2 tablets daily; not more than 2 tablets in 24 hours
children 2 to under 6 years of age | chew 1 tablet daily; not more than 1 tablet in 24 hours
children under 2 years of age | ask a doctor
consumers with liver or kidney disease | ask a doctor

Other information

- phenylketonurics: contains phenylalanine 1.25 mg per tablet.
- TAMPER EVIDENT: DO NOT USE IF BLISTER UNITS ARE TORN, BROKEN OR SHOW ANY SIGNS OF TAMPERING.
- store between 20° to 25°C (68° to 77°F).

Inactive ingredients

aspartame, citric acid anhydrous, colloidal silicon dioxide, D&C red No. 27 aluminum lake, FD&C blue No. 2 aluminum lake, flavor, magnesium stearate, mannitol, microcrystalline cellulose, sodium starch glycolate, stearic acid

Questions?

call 1-800-406-7984

Distributed By AmerisourceBergen
1300 Morris Drive, Chesterbrook, PA 19087

PRINCIPAL DISPLAY PANEL - 5 mg Tablet Blister Pack Carton

GOOD
NEIGHBOR
PHARMACY®

Compare to Children's Claritin®
Chewables active ingredient**

NDC 46122-550-60

ages 2 years and older

Non-Drowsy*
24 HOUR

Children's
loratadine chewable tablets USP, 5 mg
antihistamine

Indoor & Outdoor Allergies

Relief of:

• Sneezing • Runny Nose • Itchy, Watery Eyes • Itchy Throat or Nose

20 Chewable Tablets
The chewable tablets are to be chewed before swallowing.
*When taken as directed. See Drug Facts Panel.

actual size
grape flavor